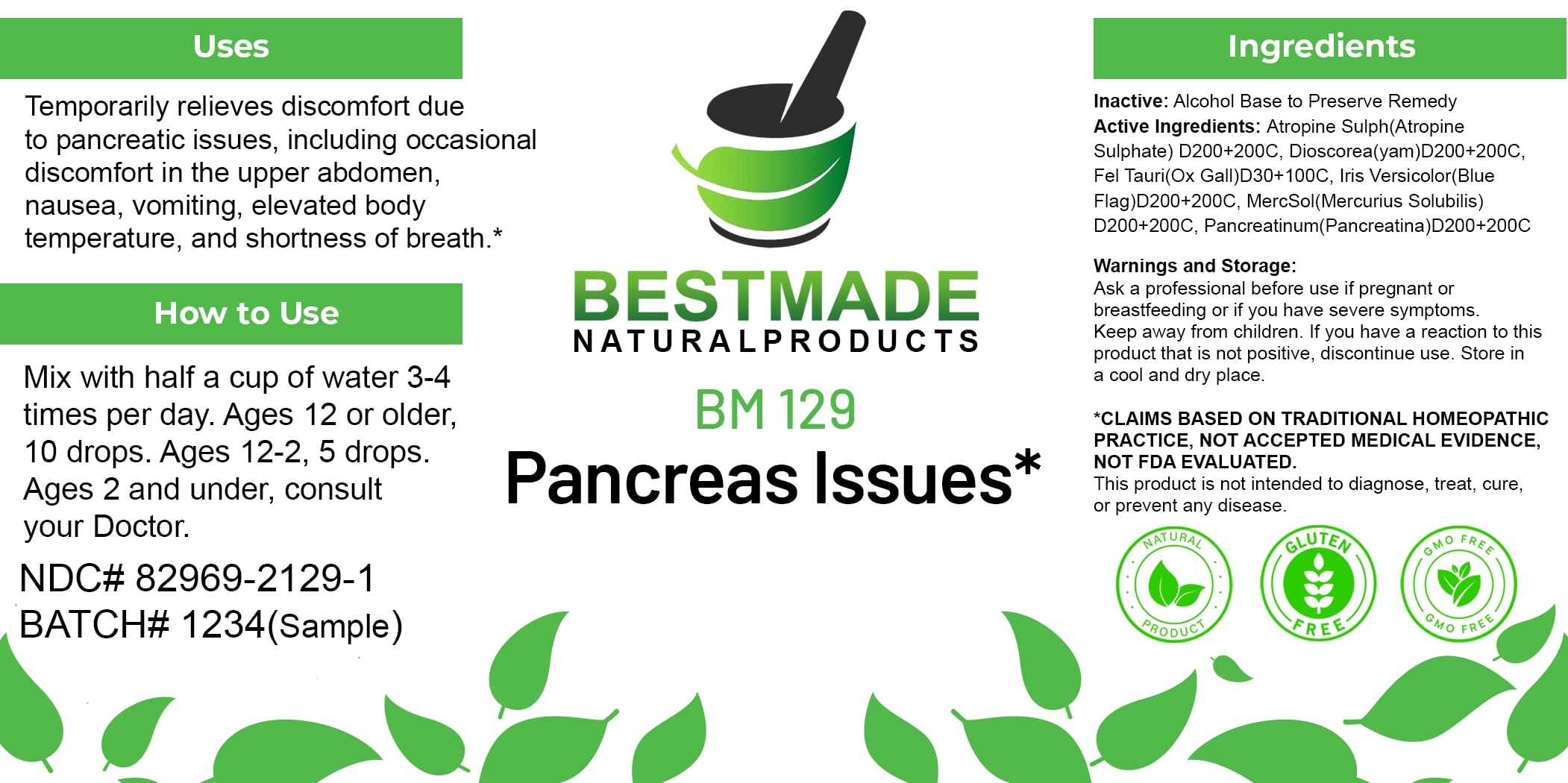 DRUG LABEL: Bestmade Natural Products BM129
NDC: 82969-2129 | Form: LIQUID
Manufacturer: Bestmade Natural Products
Category: homeopathic | Type: HUMAN OTC DRUG LABEL
Date: 20250210

ACTIVE INGREDIENTS: ATROPINE SULFATE 200 [hp_C]/200 [hp_C]; BOS TAURUS BILE 200 [hp_C]/200 [hp_C]; IRIS VERSICOLOR ROOT 200 [hp_C]/200 [hp_C]; MERCURIUS SOLUBILIS 200 [hp_C]/200 [hp_C]; DIOSCOREA VILLOSA TUBER 200 [hp_C]/200 [hp_C]; PANCRELIPASE 200 [hp_C]/200 [hp_C]
INACTIVE INGREDIENTS: ALCOHOL 200 [hp_C]/200 [hp_C]

BM129

DOSAGE AND ADMINISTRATION

How to Use

Mix with half a cup of water 3-4 times per day. Ages 12 or older, 10 drops. Ages 12-2, 5 drops. Ages 2 and under, consult your Doctor.

INACTIVE INGREDIENT

Ingredients

Inactive: Alcohol Base to Preserve Remedy

ACTIVE INGREDIENT

Active Ingredients: Atropine Sulph(Atropine Sulphate) D200+200C, Dioscorea(yam)D200+200C, Fel Tauri(Ox Gall)D30+100C, Iris Versicolor(Blue Flag)D200+200C, MercSol(Mercurius Solubilis) D200+200C, Pancreatinum(Pancreatina)D200+200C

Uses

Temporarily relieves discomfort due to pancreatic issues, including occasional discomfort in the upper abdomen, nausea, vomiting, elevated body temperature, and shortness of breath.*

*CLAIMS BASED ON TRADITIONAL HOMEOPATHIC PRACTICE, NOT ACCEPTED MEDICAL EVIDENCE, NOT FDA EVALUATED.

This product is not intended to diagnose, treat, cure, or prevent any disease.

Uses

Temporarily relieves discomfort due to pancreatic issues, including occasional discomfort in the upper abdomen, nausea, vomiting, elevated body temperature, and shortness of breath.*

*CLAIMS BASED ON TRADITIONAL HOMEOPATHIC PRACTICE, NOT ACCEPTED MEDICAL EVIDENCE, NOT FDA EVALUATED.

This product is not intended to diagnose, treat, cure, or prevent any disease.

KEEP OUT OF REACH OF CHILDREN

Warnings and Storage:

Ask a professional before use if pregnant or breastfeeding or if you have severe symptoms. Keep away from children. If you have a reaction to this product that is not positive, discontinue use. Store in a cool and dry place.

Warnings and Storage:

Ask a professional before use if pregnant or breastfeeding or if you have severe symptoms. Keep away from children. If you have a reaction to this product that is not positive, discontinue use. Store in a cool and dry place.

*CLAIMS BASED ON TRADITIONAL HOMEOPATHIC PRACTICE, NOT ACCEPTED MEDICAL EVIDENCE, NOT FDA EVALUATED.

This product is not intended to diagnose, treat, cure, or prevent any disease.

Entire package label